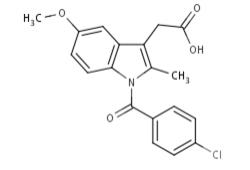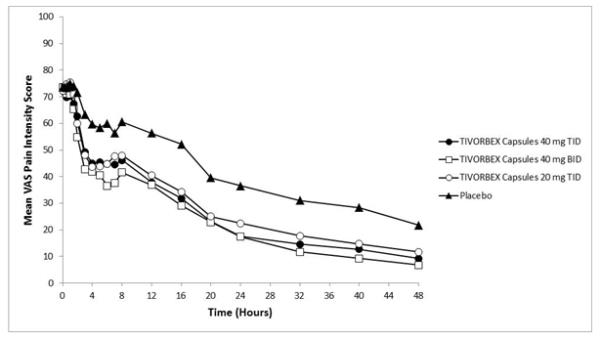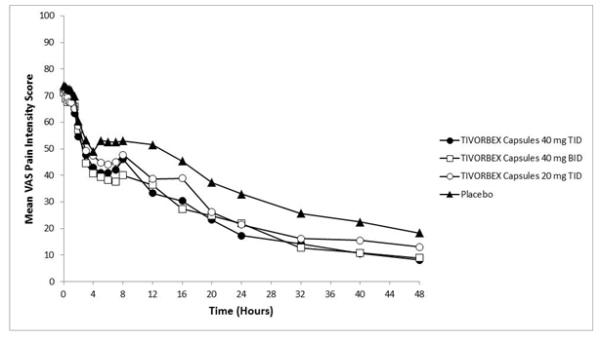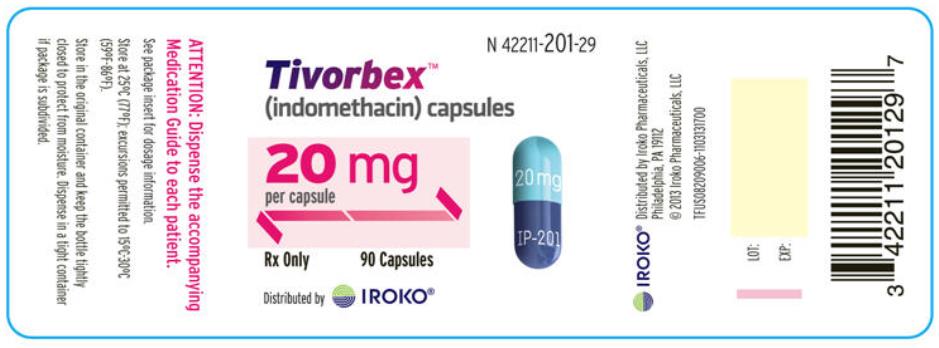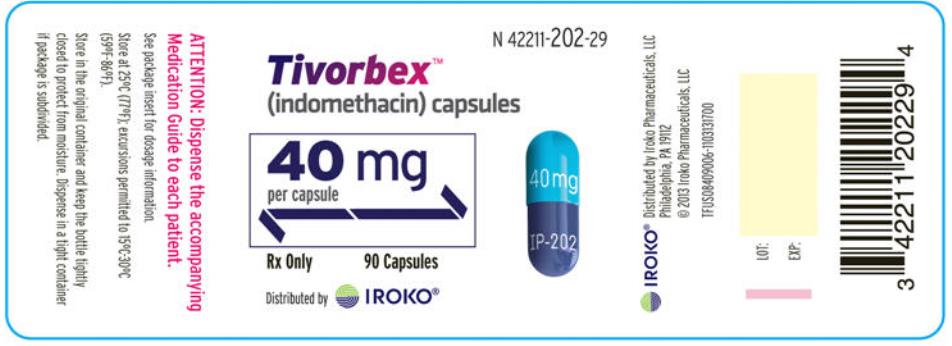 DRUG LABEL: Tivorbex
NDC: 42211-202 | Form: CAPSULE
Manufacturer: Iroko Pharmaceuticals, LLC
Category: prescription | Type: HUMAN PRESCRIPTION DRUG LABEL
Date: 20180131

ACTIVE INGREDIENTS: INDOMETHACIN 40 mg/1 1
INACTIVE INGREDIENTS: LACTOSE MONOHYDRATE; SODIUM LAURYL SULFATE; CELLULOSE, MICROCRYSTALLINE; CROSCARMELLOSE SODIUM; SODIUM STEARYL FUMARATE; GELATIN; TITANIUM DIOXIDE; FD&C BLUE NO. 1; FD&C BLUE NO. 2

HIGHLIGHTS OF PRESCRIBING INFORMATION

These highlights do not include all the information needed to use TIVORBEX® safely and effectively. See full prescribing information for TIVORBEX.
TIVORBEX (indomethacin) Capsules, for oral use
Initial U.S. Approval: 1965

RECENT MAJOR CHANGES

Boxed Warning | 5/2016
Warnings and Precautions, Cardiovascular Thrombotic Events (5.1), | 5/2016
Warnings and Precautions, Heart Failure and Edema (5.5) | 5/2016

WARNING: RISK OF SERIOUS CARDIOVASCULAR AND GASTROINTESTINAL EVENTS

See full prescribing information for complete boxed warning.

- Nonsteroidal anti-inflammatory drugs (NSAIDs) cause an increased risk of serious cardiovascular thrombotic events, including myocardial infarction and stroke, which can be fatal. This risk may occur early in treatment and may increase with duration of use (5.1)
- TIVORBEX is contraindicated in the setting of coronary artery bypass graft (CABG) surgery (4, 5.1)
- NSAIDs cause an increased risk of serious gastrointestinal (GI) adverse events including bleeding, ulceration, and perforation of the stomach or intestines, which can be fatal. These events can occur at any time during use and without warning symptoms. Elderly patients and patients with a prior history of peptic ulcer disease and/or GI bleeding are at greater risk for serious GI events (5.2)

1 INDICATIONS AND USAGE

TIVORBEX is a nonsteroidal anti-inflammatory drug indicated for treatment of mild to moderate acute pain in adults (1)

2 DOSAGE AND ADMINISTRATION

- Use the lowest effective dosage for shortest duration consistent with individual patient treatment goals (2.1)
- The dosage is 20 mg orally three times daily or 40 mg orally two or three times daily. (2.1)
- TIVORBEX capsules are not interchangeable with other formulations of oral indomethacin (2.2)

3 DOSAGE FORMS AND STRENGTHS

TIVORBEX (indomethacin) Capsules: 20 mg and 40 mg (3)

4 CONTRAINDICATIONS

- Known hypersensitivity to indomethacin or any components of the drug product (4)
- History of asthma, urticaria, or other allergic-type reactions after taking aspirin or other NSAIDs (4)
- In the setting of CABG surgery (4)

5 WARNINGS AND PRECAUTIONS

- Hepatotoxicity: Inform patients of warning signs and symptoms of hepatotoxicity. Discontinue if abnormal liver tests persist or worsen or if clinical signs and symptoms of liver disease develop (5.3)
- Hypertension: Patients taking some antihypertensive medications may have impaired response to these therapies when taking NSAIDs. Monitor blood pressure (5.4, 7)
- Heart Failure and Edema: Avoid use of TIVORBEX in patients with severe heart failure unless benefits are expected to outweigh risk of worsening heart failure (5.5)
- Renal Toxicity: Monitor renal function in patients with renal or hepatic impairment, heart failure, dehydration, or hypovolemia. Avoid use of TIVORBEX in patients with advanced renal disease unless benefits are expected to outweigh risk of worsening renal function (5.6)
- Anaphylactic Reactions: Seek emergency help if an anaphylactic reaction occurs (5.7)
- Exacerbation of Asthma Related to Aspirin Sensitivity: TIVORBEX is contraindicated in patients with aspirin-sensitive asthma. Monitor patients with preexisting asthma (without aspirin sensitivity) (5.8)
- Serious Skin Reactions: Discontinue TIVORBEX at first appearance of skin rash or other signs of hypersensitivity (5.9)
- Premature Closure of Fetal Ductus Arteriosus: Avoid use in pregnant women starting at 30 weeks gestation (5.10, 8.1)
- Hematologic Toxicity: Monitor hemoglobin or hematocrit in patients with any signs or symptoms of anemia (5.11, 7)

6 ADVERSE REACTIONS

Most common adverse reactions (incidence ≥2% in TIVORBEX 20 mg and 40 mg groups) are nausea, post procedural edema, headache, dizziness, vomiting, post procedural hemorrhage, constipation, pruritus, diarrhea, dyspepsia, post procedural swelling, presyncope, rash, abdominal pain (upper), somnolence, pruritus generalized, hyperhidrosis, decreased appetite, hot flush and syncope. (6.1)

To report SUSPECTED ADVERSE REACTIONS, contact Iroko Pharmaceuticals, LLC at 1-877-757-0676 or FDA at 1-800-FDA-1088 or www.fda.gov/medwatch.

7 DRUG INTERACTIONS

- Drugs that Interfere with Hemostasis (e.g. warfarin, aspirin, SSRIs/SNRIs): Monitor patients for bleeding who are concomitantly taking TIVORBEX with drugs that interfere with hemostasis. Concomitant use of TIVORBEX and analgesic doses of aspirin is not generally recommended (7)
- ACE Inhibitors, Angiotensin Receptor Blockers (ARB), or Beta-Blockers: Concomitant use with TIVORBEX may diminish the antihypertensive effect of these drugs. Monitor blood pressure (7)
- ACE Inhibitors and ARBs: Concomitant use with TIVORBEX in elderly, volume depleted, or those with renal impairment may result in deterioration of renal function. In such high risk patients, monitor for signs of worsening renal function (7)
- Diuretics: NSAIDs can reduce natriuretic effect of furosemide and thiazide diuretics. Monitor patients to assure diuretic efficacy including antihypertensive effects (7)
- Digoxin: Concomitant use with TIVORBEX can increase serum concentration and prolong half-life of digoxin. Monitor serum digoxin levels (7)

8 USE IN SPECIFIC POPULATIONS

Pregnancy: Use of NSAIDs during the third trimester of pregnancy increases the risk of premature closure of the fetal ductus arteriosus. Avoid use of NSAIDs in pregnant women starting at 30 weeks gestation (5.10, 8.1)

Infertility: NSAIDs are associated with reversible infertility. Consider withdrawal of TIVORBEX in women who have difficulties conceiving (8.3)

FULL PRESCRIBING INFORMATION

WARNING: RISK OF SERIOUS CARDIOVASCULAR AND GASTROINTESTINAL EVENTS

Cardiovascular Thrombotic Events

- Nonsteroidal anti-inflammatory drugs (NSAIDs) cause an increased risk of serious cardiovascular thrombotic events, including myocardial infarction and stroke, which can be fatal. This risk may occur early in treatment and may increase with duration of use [see Warnings and Precautions (5.1)].
- TIVORBEX is contraindicated in the setting of coronary artery bypass graft (CABG) surgery [see Contraindications (4) and Warnings and Precautions (5.1)].

Gastrointestinal Bleeding, Ulceration, and Perforation

- NSAIDs cause an increased risk of serious gastrointestinal (GI) adverse events including bleeding, ulceration, and perforation of the stomach or intestines, which can be fatal. These events can occur at any time during use and without warning symptoms. Elderly patients and patients with a prior history of peptic ulcer disease and/or GI bleeding are at greater risk for serious GI events [see Warnings and Precautions (5.2)].

1 INDICATIONS AND USAGE

TIVORBEX is indicated for treatment of mild to moderate acute pain in adults.

2 DOSAGE AND ADMINISTRATION

2.1 General Dosing Instructions

Carefully consider the potential benefits and risks of TIVORBEX and other treatment options before deciding to use TIVORBEX. Use the lowest effective dosage for the shortest duration consistent with individual patient treatment goals [see Warnings and Precautions (5)].

For treatment of mild to moderate acute pain, the dosage is 20 mg three times daily or 40 mg two or three times daily.

2.2 Non-Interchangeability with Other Formulations of Indomethacin

Different dose strengths and formulations of oral indomethacin are not interchangeable. This difference should be taken into consideration when changing strengths or formulations.

3 DOSAGE FORMS AND STRENGTHS

TIVORBEX (indomethacin) Capsules 20 mg – dark blue body and light blue cap (imprinted IP-201 on the body and 20 mg on the cap in white ink).

TIVORBEX (indomethacin) Capsules 40 mg – dark blue body and blue cap (imprinted IP-202 on the body and 40 mg on the cap in white ink).

4 CONTRAINDICATIONS

TIVORBEX is contraindicated in the following patients:

- Known hypersensitivity (e.g., anaphylactic reactions and serious skin reactions) to indomethacin or any components of the drug product [see Warnings and Precautions (5.7, 5.9)]
- History of asthma, urticaria, or other allergic-type reactions after taking aspirin or other NSAIDs. Severe, sometimes fatal, anaphylactic reactions to NSAIDs have been reported in such patients [see Warnings and Precautions (5.7, 5.8)]
- In the setting of coronary artery bypass graft (CABG) surgery [see Warnings and Precautions (5.1)]

5 WARNINGS AND PRECAUTIONS

5.1 Cardiovascular Thrombotic Events

Clinical trials of several COX-2 selective and nonselective NSAIDs of up to three years duration have shown an increased risk of serious cardiovascular (CV) thrombotic events, including myocardial infarction (MI) and stroke, which can be fatal. Based on available data, it is unclear that the risk for CV thrombotic events is similar for all NSAIDs. The relative increase in serious CV thrombotic events over baseline conferred by NSAID use appears to be similar in those with and without known CV disease or risk factors for CV disease. However, patients with known CV disease or risk factors had a higher absolute incidence of excess serious CV thrombotic events, due to their increased baseline rate. Some observational studies found that this increased risk of serious CV thrombotic events began as early as the first weeks of treatment. The increase in CV thrombotic risk has been observed most consistently at higher doses.

To minimize the potential risk for an adverse CV event in NSAID-treated patients, use the lowest effective dose for the shortest duration possible. Physicians and patients should remain alert for the development of such events, throughout the entire treatment course, even in the absence of previous CV symptoms. Patients should be informed about the symptoms of serious CV events and the steps to take if they occur.

There is no consistent evidence that concurrent use of aspirin mitigates the increased risk of serious CV thrombotic events associated with NSAID use. The concurrent use of aspirin and an NSAID, such as indomethacin, increases the risk of serious gastrointestinal (GI) events [see Warnings and Precautions (5.2)].

Status Post Coronary Artery Bypass Graft (CABG) Surgery

Two large, controlled clinical trials of a COX-2 selective NSAID for the treatment of pain in the first 10–14 days following CABG surgery found an increased incidence of myocardial infarction and stroke. NSAIDs are contraindicated in the setting of CABG [see Contraindications (4)].

Post-MI Patients

Observational studies conducted in the Danish National Registry have demonstrated that patients treated with NSAIDs in the post-MI period were at increased risk of reinfarction, CV-related death, and all-cause mortality beginning in the first week of treatment. In this same cohort, the incidence of death in the first year post-MI was 20 per 100 person years in NSAID-treated patients compared to 12 per 100 person years in non-NSAID exposed patients. Although the absolute rate of death declined somewhat after the first year post-MI, the increased relative risk of death in NSAID users persisted over at least the next four years of follow-up.

Avoid the use of TIVORBEX in patients with a recent MI unless the benefits are expected to outweigh the risk of recurrent CV thrombotic events. If TIVORBEX is used in patients with a recent MI, monitor patients for signs of cardiac ischemia.

5.2 Gastrointestinal Bleeding, Ulceration, and Perforation

NSAIDs, including indomethacin, cause serious gastrointestinal (GI) adverse events including inflammation, bleeding, ulceration, and perforation of the esophagus, stomach, small intestine, or large intestine, which can be fatal. These serious adverse events can occur at any time, with or without warning symptoms, in patients treated with NSAIDs. Only one in five patients who develop a serious upper GI adverse event on NSAID therapy is symptomatic. Upper GI ulcers, gross bleeding, or perforation caused by NSAIDs occurred in approximately 1% of patients treated for 3-6 months, and in about 2%-4% of patients treated for one year. However, even short-term NSAID therapy is not without risk.

Risk Factors for GI Bleeding, Ulceration, and Perforation

Patients with a prior history of peptic ulcer disease and/or GI bleeding who used NSAIDs had a greater than 10-fold increased risk for developing a GI bleed compared to patients without these risk factors. Other factors that increase the risk of GI bleeding in patients treated with NSAIDs include longer duration of NSAID therapy; concomitant use of oral corticosteroids, aspirin, anticoagulants, or selective serotonin reuptake inhibitors (SSRIs); smoking; use of alcohol; older age; and poor general health status. Most postmarketing reports of fatal GI events occurred in elderly or debilitated patients. Additionally, patients with advanced liver disease and/or coagulopathy are at increased risk for GI bleeding.

Strategies to Minimize the GI Risks in NSAID-treated patients:

- Use the lowest effective dosage for the shortest possible duration.
- Avoid administration of more than one NSAID at a time.
- Avoid use in patients at higher risk unless benefits are expected to outweigh the increased risk of bleeding. For such patients, as well as those with active GI bleeding, consider alternate therapies other than NSAIDs.
- Remain alert for signs and symptoms of GI ulceration and bleeding during NSAID therapy.
- If a serious GI adverse event is suspected, promptly initiate evaluation and treatment, and discontinue TIVORBEX until a serious GI adverse event is ruled out.
- In the setting of concomitant use of low-dose aspirin for cardiac prophylaxis, monitor patients more closely for evidence of GI bleeding [see Drug Interactions (7)].

5.3 Hepatotoxicity

Elevations of ALT or AST (three or more times the upper limit of normal [ULN]) have been reported in approximately 1% of NSAID-treated patients in clinical trials. In addition, rare, sometimes fatal, cases of severe hepatic injury, including fulminant hepatitis, liver necrosis, and hepatic failure have been reported.

Elevations of ALT or AST (less than three times ULN) may occur in up to 15% of patients treated with NSAIDs including indomethacin.

Inform patients of the warning signs and symptoms of hepatotoxicity (e.g., nausea, fatigue, lethargy, diarrhea, pruritus, jaundice, right upper quadrant tenderness, and "flu-like" symptoms). If clinical signs and symptoms consistent with liver disease develop, or if systemic manifestations occur (e.g., eosinophilia, rash, etc.), discontinue TIVORBEX immediately, and perform a clinical evaluation of the patient.

5.4 Hypertension

NSAIDs, including TIVORBEX, can lead to new onset of hypertension or worsening of preexisting hypertension, either of which may contribute to the increased incidence of CV events. Patients taking angiotensin converting enzyme (ACE) inhibitors, thiazide diuretics, or loop diuretics may have impaired response to these therapies when taking NSAIDs [see Drug Interactions (7)].

Monitor blood pressure (BP) during the initiation of NSAID treatment and throughout the course of therapy.

5.5 Heart Failure and Edema

The Coxib and traditional NSAID Trialists’ Collaboration meta-analysis of randomized controlled trials demonstrated an approximately two-fold increase in hospitalizations for heart failure in COX-2 selective-treated patients and nonselective NSAID-treated patients compared to placebo-treated patients. In a Danish National Registry study of patients with heart failure, NSAID use increased the risk of MI, hospitalization for heart failure, and death.

Additionally, fluid retention and edema have been observed in some patients treated with NSAIDs. Use of indomethacin may blunt the CV effects of several therapeutic agents used to treat these medical conditions (e.g., diuretics, ACE inhibitors, or angiotensin receptor blockers [ARBs]) [see Drug Interactions (7)].

Avoid the use of TIVORBEX in patients with severe heart failure unless the benefits are expected to outweigh the risk of worsening heart failure. If TIVORBEX is used in patients with severe heart failure, monitor patients for signs of worsening heart failure.

5.6 Renal Toxicity and Hyperkalemia

Renal Toxicity

Long-term administration of NSAIDs has resulted in renal papillary necrosis and other renal injury.

Renal toxicity has also been seen in patients in whom renal prostaglandins have a compensatory role in the maintenance of renal perfusion. In these patients, administration of an NSAID may cause a dose-dependent reduction in prostaglandin formation and, secondarily, in renal blood flow, which may precipitate overt renal decompensation. Patients at greatest risk of this reaction are those with impaired renal function, dehydration, hypovolemia, heart failure, liver dysfunction, those taking diuretics and ACE inhibitors or ARBs, and the elderly. Discontinuation of NSAID therapy is usually followed by recovery to the pretreatment state.

No information is available from controlled clinical studies regarding the use of TIVORBEX in patients with advanced renal disease. The renal effects of TIVORBEX may hasten the progression of renal dysfunction in patients with preexisting renal disease.

Correct volume status in dehydrated or hypovolemic patients prior to initiating TIVORBEX. Monitor renal function in patients with renal or hepatic impairment, heart failure, dehydration, or hypovolemia during use of TIVORBEX [see Drug Interactions (7)]. Avoid the use of TIVORBEX in patients with advanced renal disease unless the benefits are expected to outweigh the risk of worsening renal function. If TIVORBEX is used in patients with advanced renal disease, monitor patients for signs of worsening renal function.

It has been reported that the addition of the potassium-sparing diuretic, triamterene, to a maintenance schedule of indomethacin resulted in reversible acute renal failure in two of four healthy volunteers. Indomethacin and triamterene should not be administered together.

Hyperkalemia

Increases in serum potassium concentration, including hyperkalemia, have been reported with use of NSAIDs, even in some patients without renal impairment. In patients with normal renal function, these effects have been attributed to a hyporeninemic-hypoaldosteronism state.

Both indomethacin and potassium-sparing diuretics may be associated with increased serum potassium levels. The potential effects of indomethacin and potassium-sparing diuretics on potassium levels and renal function should be considered when these agents are administered concurrently.

5.7 Anaphylactic Reactions

Indomethacin has been associated with anaphylactic reactions in patients with and without known hypersensitivity to indomethacin and in patients with aspirin-sensitive asthma [see Contraindications (4) and Warnings and Precautions (5.8)].

Seek emergency help if an anaphylactic reaction occurs.

5.8 Exacerbation of Asthma Related to Aspirin Sensitivity

A subpopulation of patients with asthma may have aspirin-sensitive asthma which may include chronic rhinosinusitis complicated by nasal polyps; severe, potentially fatal bronchospasm; and/or intolerance to aspirin and other NSAIDs. Because cross-reactivity between aspirin and other NSAIDs has been reported in such aspirin-sensitive patients, TIVORBEX is contraindicated in patients with this form of aspirin sensitivity [see Contraindications (4)]. When TIVORBEX is used in patients with preexisting asthma (without known aspirin sensitivity), monitor patients for changes in the signs and symptoms of asthma.

5.9 Serious Skin Reactions

NSAIDs, including indomethacin, can cause serious skin adverse reactions such as exfoliative dermatitis, Stevens-Johnson Syndrome (SJS), and toxic epidermal necrolysis (TEN), which can be fatal. These serious events may occur without warning. Inform patients about the signs and symptoms of serious skin reactions, and to discontinue the use of TIVORBEX at the first appearance of skin rash or any other sign of hypersensitivity. TIVORBEX is contraindicated in patients with previous serious skin reactions to NSAIDs [see Contraindications (4)].

5.10 Premature Closure of Fetal Ductus Arteriosus

Indomethacin may cause premature closure of the fetal ductus arteriosus. Avoid use of NSAIDs, including TIVORBEX, in pregnant women starting at 30 weeks of gestation (third trimester) [see Use in Specific Populations (8.1)].

5.11 Hematologic Toxicity

Anemia has occurred in NSAID-treated patients. This may be due to occult or gross blood loss, fluid retention, or an incompletely described effect on erythropoiesis. If a patient treated with TIVORBEX has any signs or symptoms of anemia, monitor hemoglobin or hematocrit.

NSAIDs, including TIVORBEX, may increase the risk of bleeding events. Co-morbid conditions, such as coagulation disorders, or concomitant use of warfarin, other anticoagulants, antiplatelet agents (e.g., aspirin), serotonin reuptake inhibitors (SSRIs) and serotonin norepinephrine reuptake inhibitors (SNRIs) may increase this risk. Monitor these patients for signs of bleeding [see Drug Interactions (7)].

5.12 Masking of Inflammation and Fever

The pharmacological activity of TIVORBEX in reducing inflammation, and possibly fever, may diminish the utility of diagnostic signs in detecting infections.

5.13 Laboratory Monitoring

Because serious GI bleeding, hepatotoxicity, and renal injury can occur without warning symptoms or signs, consider monitoring patients on long-term NSAID treatment with a CBC and a chemistry profile periodically [see Warnings and Precautions (5.2, 5.3, 5.6)].

5.14 Central Nervous System Effects

TIVORBEX may aggravate depression or other psychiatric disturbances, epilepsy, and parkinsonism, and should be used with considerable caution in patients with these conditions. Discontinue TIVORBEX if severe CNS adverse reactions develop.

TIVORBEX may cause drowsiness; therefore, caution patients about engaging in activities requiring mental alertness and motor coordination, such as driving a car. Indomethacin may also cause headache. Headache which persists despite dosage reduction requires cessation of therapy with TIVORBEX.

5.15 Ocular Effects

Corneal deposits and retinal disturbances, including those of the macula, have been observed in some patients who had received prolonged therapy with TIVORBEX. Be alert to the possible association between the changes noted and TIVORBEX. It is advisable to discontinue therapy if such changes are observed. Blurred vision may be a significant symptom and warrants a thorough ophthalmological examination. Since these changes may be asymptomatic, ophthalmologic examination at periodic intervals is desirable in patients receiving prolonged therapy. TIVORBEX is not indicated for long-term treatment.

6 ADVERSE REACTIONS

The following adverse reactions are discussed in greater detail in other sections of the labeling:

- Cardiovascular Thrombotic Events [see Warnings and Precautions (5.1)]
- GI Bleeding, Ulceration and Perforation [see Warnings and Precautions (5.2)]
- Hepatotoxicity [see Warnings and Precautions (5.3)]
- Hypertension [see Warnings and Precautions (5.4)]
- Heart Failure and Edema [see Warnings and Precautions (5.5)]
- Renal Toxicity and Hyperkalemia [see Warnings and Precautions (5.6)]
- Anaphylactic Reactions [see Warnings and Precautions (5.7)]
- Serious Skin Reactions [see Warnings and Precautions (5.9)]
- Hematologic Toxicity [see Warnings and Precautions (5.11)]

6.1 Clinical Trials Experience

Because clinical trials are conducted under widely varying conditions, adverse reaction rates observed in the clinical trials of a drug cannot be directly compared to rates in the clinical trials of another drug and may not reflect the rates observed in clinical practice.

Five hundred and fifty-four patients (554) received TIVORBEX 20 mg or 40 mg for up to 48 hours in two double-blind, placebo-controlled, clinical trials of acute pain following bunionectomy. The most frequent adverse reactions in these trials are summarized below.

Table 1 Summary of Adverse Reactions (≥2% in TIVORBEX 20 mg or 40 mg group) - Phase 3 Studies in Patients With Postsurgical Pain
Any Treatment Emergent AE | TIVORBEX 40 mg three times daily* (%) N=187 | TIVORBEX 40 mg twice daily* (%) N=184 | TIVORBEX 20 mg three times daily* (%) N=183 | Placebo* (%) N=188
Nausea | 33 | 33 | 34 | 36
Post procedural edema | 24 | 22 | 26 | 32
Headache | 16 | 14 | 11 | 11
Dizziness | 15 | 14 | 10 | 17
Vomiting | 8 | 10 | 12 | 11
Post procedural hemorrhage | 5 | 11 | 5 | 6
Constipation | 4 | 5 | 6 | 5
Pruritus | 2 | 3 | 4 | 0
Diarrhea | 2 | 3 | 2 | 1
Dyspepsia | 3 | 2 | 1 | 1
Post procedural swelling | 1 | 3 | 1 | 1
Presyncope | 2 | 3 | 1 | 2
Rash | 2 | 1 | 2 | 0
Abdominal pain, upper | 2 | 1 | 2 | 1
Somnolence | 2 | 2 | 1 | 1
Pruritus generalized | 1 | 2 | 1 | 0
Hyperhidrosis | 0 | 2 | 1 | 1
Decreased appetite | 0 | 2 | 1 | 1
Hot flush | 0 | 1 | 2 | 1
Syncope | 0 | 2 | 1 | 1
* One tablet of hydrocodone/acetaminophen 10 mg/325 mg was permitted every 4 to 6 hours as rescue medication for pain management. There was a greater use of concomitant opioid rescue medication in placebo-treated patients than in TIVORBEX-treated patients [see Clinical Studies (14)].

6.2 Postmarketing Experience

The following adverse reactions have been identified during post approval use of indomethacin. Because these reactions are reported voluntarily from a population of uncertain size, it is not always possible to reliably estimate their frequency or establish a causal relationship to drug exposure.

Gastrointestinal: anorexia, bloating (includes distension), flatulence, peptic ulcer, gastroenteritis, rectal bleeding, proctitis, single or multiple ulcerations, including perforation and hemorrhage of the esophagus, stomach, duodenum or small and large intestines intestinal ulceration associated with stenosis and obstruction, gastrointestinal bleeding without obvious ulcer formation and perforation of preexisting sigmoid lesions (diverticulum, carcinoma, etc) development of ulcerative colitis and regional ileitis ulcerative stomatitis, toxic hepatitis and jaundice (some fatal cases have been reported), intestinal strictures (diaphragms), pancreatitis.

Cardiovascular: hypertension, hypotension, tachycardia, chest pain, congestive heart failure, arrhythmia, palpitations.

Hematologic: leukopenia, bone marrow depression, anemia secondary to obvious or occult gastrointestinal bleeding, aplastic anemia, hemolytic anemia, agranulocytosis, thrombocytopenic purpura, disseminated intravascular coagulation.

Central Nervous System: anxiety (includes nervousness), muscle weakness, involuntary muscle movements, insomnia, confusion, psychic disturbances including psychotic episodes, mental confusion, drowsiness, light-headedness, syncope, paresthesia, aggravation of epilepsy and parkinsonism, depersonalization, coma, peripheral neuropathy, convulsion, dysarthria.

Hypersensitivity: acute anaphylaxis, acute respiratory distress rapid fall in blood pressure resembling a shock-like state, angioedema, dyspnea, asthma, purpura, angiitis, pulmonary edema, fever.

Metabolic: edema, weight gain, fluid retention, flushing or sweating, hyperglycemia, glycosuria, hyperkalemia

Genitourinary: hematuria, vaginal bleeding, proteinuria, nephrotic syndrome, interstitial nephritis: BUN elevation, renal insufficiency, including renal failure.

Special Senses: ocular — corneal deposits and retinal disturbances, including those of the macula, have been reported in some patients on prolonged therapy with indomethacin; blurred vision, diplopia, hearing disturbances, deafness.

Skin and Appendages: pruritus, rash, urticaria, petechiae or ecchymosis, exfoliative dermatitis, erythema nodosum, loss of hair, Stevens-Johnson syndrome, erythema multiforme, toxic epidermal necrolysis.

Miscellaneous: epistaxis, breast changes, including enlargement and tenderness, gynecomastia

Causal relationship unknown

Other reactions have been reported but occurred under circumstances where a causal relationship could not be established. However, in these rarely reported events, the possibility cannot be excluded. Therefore, these observations are being listed to serve as alerting information to physicians:

Cardiovascular: Thrombophlebitis

Hematologic: Although there have been several reports of leukemia, the supporting information is weak

Genitourinary: Urinary frequency

Musculoskeletal and Connective Tissue: A rare occurrence of fulminant necrotizing fasciitis, particularly in association with Group Ab hemolytic streptococcus, has been described in persons treated with nonsteroidal anti-inflammatory agents, including indomethacin, sometimes with fatal outcome [see Warnings and Precautions (5.9)].

7 DRUG INTERACTIONS

See Table 2 for clinically significant drug interactions with indomethacin.

Table 2 Clinically Significant Drug Interactions with Indomethacin
Drugs That Interfere with Hemostasis
Clinical Impact: | - Indomethacin and anticoagulants such as warfarin have a synergistic effect on bleeding. The concomitant use of indomethacin and anticoagulants have an increased risk of serious bleeding compared to the use of either drug alone. - Serotonin release by platelets plays an important role in hemostasis. Case-control and cohort epidemiological studies showed that concomitant use of drugs that interfere with serotonin reuptake and an NSAID may potentiate the risk of bleeding more than an NSAID alone.
Intervention: | Monitor patients with concomitant use of TIVORBEX with anticoagulants (e.g., warfarin), antiplatelet agents (e.g., aspirin), selective serotonin reuptake inhibitors (SSRIs), and serotonin norepinephrine reuptake inhibitors (SNRIs) for signs of bleeding [see Warnings and Precautions (5.11)].
Aspirin
Clinical Impact: | Controlled clinical studies showed that the concomitant use of NSAIDs and analgesic doses of aspirin does not produce any greater therapeutic effect than the use of NSAIDs alone. In a clinical study, the concomitant use of an NSAID and aspirin was associated with a significantly increased incidence of GI adverse reactions as compared to use of the NSAID alone [see Warnings and Precautions (5.2)].
Intervention: | Concomitant use of TIVORBEX and analgesic doses of aspirin is not generally recommended because of the increased risk of bleeding [see Warnings and Precautions (5.11)]. TIVORBEX is not a substitute for low dose aspirin for cardiovascular protection
ACE Inhibitors, Angiotensin Receptor Blockers, and Beta-Blockers
Clinical Impact: | - NSAIDs may diminish the antihypertensive effect of angiotensin converting enzyme (ACE) inhibitors, angiotensin receptor blockers (ARBs), or beta-blockers (including propranolol). - In patients who are elderly, volume-depleted (including those on diuretic therapy), or have renal impairment, co-administration of an NSAID with ACE inhibitors or ARBs may result in deterioration of renal function, including possible acute renal failure. These effects are usually reversible.
Intervention: | - During concomitant use of TIVORBEX and ACE-inhibitors, ARBs, or beta-blockers, monitor blood pressure to ensure that the desired blood pressure is obtained. - During concomitant use of TIVORBEX and ACE-inhibitors or ARBs in patients who are elderly, volume-depleted, or have impaired renal function, monitor for signs of worsening renal function [see Warnings and Precautions (5.6)]. - When these drugs are administered concomitantly, patients should be adequately hydrated. Assess renal function at the beginning of the concomitant treatment and periodically thereafter.
Diuretics
Clinical Impact: | Clinical studies, as well as post-marketing observations, showed that NSAIDs reduced the natriuretic effect of loop diuretics (e.g., furosemide) and thiazide diuretics in some patients. This effect has been attributed to the NSAID inhibition of renal prostaglandin synthesis. It has been reported that the addition of triamterene to a maintenance schedule of indomethacin resulted in reversible acute renal failure in two of four healthy volunteers. Indomethacin and triamterene should not be administered together. Both indomethacin and potassium-sparing diuretics may be associated with increased serum potassium levels. The potential effects of indomethacin and potassium-sparing diuretics on potassium levels and renal function should be considered when these agents are administered concurrently [see Warnings and Precautions (5.6)].
Intervention: | Indomethacin and triamterene should not be administered together. During concomitant use of TIVORBEX with diuretics, observe patients for signs of worsening renal function, in addition to assuring diuretic efficacy including antihypertensive effects. Be aware that indomethacin and potassium-sparing diuretics may both be associated with increased serum potassium levels [see Warnings and Precautions (5.6)].
Digoxin
Clinical Impact: | The concomitant use of indomethacin with digoxin has been reported to increase the serum concentration and prolong the half-life of digoxin.
Intervention: | During concomitant use of TIVORBEX and digoxin, monitor serum digoxin levels.
Lithium
Clinical Impact: | NSAIDs have produced elevations in plasma lithium levels and reductions in renal lithium clearance. The mean minimum lithium concentration increased 15%, and the renal clearance decreased by approximately 20%. This effect has been attributed to NSAID inhibition of renal prostaglandin synthesis.
Intervention: | During concomitant use of TIVORBEX and lithium, monitor patients for signs of lithium toxicity.
Methotrexate
Clinical Impact: | Concomitant use of NSAIDs and methotrexate may increase the risk for methotrexate toxicity (e.g., neutropenia, thrombocytopenia, renal dysfunction).
Intervention: | During concomitant use of TIVORBEX and methotrexate, monitor patients for methotrexate toxicity.
Cyclosporine
Clinical Impact: | Concomitant use of TIVORBEX and cyclosporine may increase cyclosporine’s nephrotoxicity.
Intervention: | During concomitant use of TIVORBEX and cyclosporine, monitor patients for signs of worsening renal function.
NSAIDs and Salicylates
Clinical Impact: | Concomitant use of indomethacin with other NSAIDs or salicylates (e.g., diflunisal, salsalate) increases the risk of GI toxicity, with little or no increase in efficacy [see Warnings and Precautions (5.2)]. Combined use with diflunisal may be particularly hazardous because diflunisal causes significantly higher plasma levels of indomethacin. [see Clinical Pharmacology (12.3)]. In some patients, combined use of indomethacin and diflunisal has been associated with fatal gastrointestinal hemorrhage.
Intervention: | The concomitant use of indomethacin with other NSAIDs or salicylates , especially diflunisal, is not recommended.
Pemetrexed
Clinical Impact: | Concomitant use of TIVORBEX and pemetrexed may increase the risk of pemetrexed-associated myelosuppression, renal, and GI toxicity (see the pemetrexed prescribing information).
Intervention: | During concomitant use of TIVORBEX and pemetrexed, in patients with renal impairment whose creatinine clearance ranges from 45 to 79 mL/min, monitor for myelosuppression, renal and GI toxicity. NSAIDs with short elimination half-lives (e.g., diclofenac, indomethacin) should be avoided for a period of two days before, the day of, and two days following administration of pemetrexed. In the absence of data regarding potential interaction between pemetrexed and NSAIDs with longer half-lives (e.g., meloxicam, nabumetone), patients taking these NSAIDs should interrupt dosing for at least five days before, the day of, and two days following pemetrexed administration.
Probenecid
Clinical Impact | When indomethacin is given to patients receiving probenecid, the plasma levels of indomethacin are likely to be increased.
Intervention | During the concomitant use of TIVORBEX and probenecid, a lower total daily dosage of indomethacin may produce a satisfactory therapeutic effect. When increases in the dose of indomethacin are made, they should be made carefully and in small increments.

Effects on Laboratory Tests

Indomethacin reduces basal plasma renin activity (PRA), as well as those elevations of PRA induced by furosemide administration, or salt or volume depletion. These facts should be considered when evaluating plasma renin activity in hypertensive patients.

False-negative results in the dexamethasone suppression test (DST) in patients being treated with indomethacin have been reported. Thus, results of the DST should be interpreted with caution in these patients.

8 USE IN SPECIFIC POPULATIONS

8.1 Pregnancy

Pregnancy Category C in the first and second trimesters of pregnancy; Category D in the third trimester.

Risk Summary

Use of NSAIDs, including TIVORBEX, during the third trimester of pregnancy increases the risk of premature closure of the fetal ductus arteriosus. Avoid use of NSAIDs, including TIVORBEX, in pregnant women starting at 30 weeks of gestation (third trimester).

There are no adequate and well-controlled studies of TIVORBEX in pregnant women.

Data from observational studies regarding potential embryofetal risks of NSAID use in women in the first or second trimesters of pregnancy are inconclusive. In the general U.S. population, all clinically recognized pregnancies, regardless of drug exposure, have a background rate of 2-4% for major malformations, and 15-20% for pregnancy loss. In animal reproduction studies, retarded fetal ossification was observed with administration of indomethacin to mice and rats during organogenesis at doses 0.16 and 0.32 times, respectively, the maximum recommended human dose (MRHD, 120 mg). In published studies in pregnant mice, indomethacin produced maternal toxicity and death, increased fetal resorptions, and fetal malformations at 0.2 times the MRHD. When rat and mice dams were dosed during the last three days of gestation, indomethacin produced neuronal necrosis in the offspring at 0.1 and 0.05 times the MRHD, respectively [see Data]. Based on animal data, prostaglandins have been shown to have an important role in endometrial vascular permeability, blastocyst implantation, and decidualization. In animal studies, administration of prostaglandin synthesis inhibitors such as indomethacin, resulted in increased pre- and post-implantation loss.

Clinical Considerations

Labor or Delivery

There are no studies on the effects of TIVORBEX during labor or delivery. In animal studies, NSAIDs, including indomethacin, inhibit prostaglandin synthesis, cause delayed parturition, and increase the incidence of stillbirth.

Data

Animal data

Reproductive studies were conducted in mice and rats at dosages of 0.5, 1.0, 2.0, and 4.0 mg/kg/day. Except for retarded fetal ossification at 4 mg/kg/day (0.16 times [mice] and 0.32 times [rats] the MRHD on a mg/m^2 basis, respectively) considered secondary to the decreased average fetal weights, no increase in fetal malformations was observed as compared with control groups. Other studies in mice reported in the literature using higher doses (5 to 15 mg/kg/day, 0.20 to 0.60 times MRHD on a mg/m^2 basis) have described maternal toxicity and death, increased fetal resorptions, and fetal malformations.

In rats and mice, maternal indomethacin administration of 4.0 mg/kg/day (0.32 and 0.16 times the MRHD on a mg/m^2 basis) during the last 3 days of gestation was associated with an increased incidence of neuronal necrosis in the diencephalon in the live-born fetuses however no increase in neuronal necrosis was observed at 2.0 mg/kg/day as compared to the control groups (0.16 and 0.08 times the MRHD on a mg/m^2 basis). Administration of 0.5 or 4.0 mg/kg/day to offspring during the first 3 days of life did not cause an increase in neuronal necrosis at either dose level.

8.2 Lactation

Risk Summary

Based on available published clinical data, indomethacin may be present in human milk. The developmental and health benefits of breastfeeding should be considered along with the mother’s clinical need for TIVORBEX and any potential adverse effects on the breastfed infant from the TIVORBEX or from the underlying maternal condition.

Data

In one study, levels of indomethacin in breast milk were below the sensitivity of the assay (<20 mcg/L) in 11 of 15 women using doses ranging from 75 mg orally to 300 mg rectally daily (0.94 to 4.29 mg/kg daily) in the postpartum period. Based on these levels, the average concentration present in breast milk was estimated to be 0.27% of the maternal weight-adjusted dose. In another study indomethacin levels were measured in breast milk of eight postpartum women using doses of 75 mg daily and the results were used to calculate an estimated infant daily dose. The estimated infant dose of indomethacin from breast milk was less than 30 mcg/day or 4.5 mcg/kg/day assuming breast milk intake of 150 mL/kg/day. This is 0.5% of the maternal weight-adjusted dosage or about 3% of the neonatal dose for treatment of patent ductus arteriosus.

8.3 Females and Males of Reproductive Potential

Infertility

Females

Based on the mechanism of action, the use of prostaglandin-mediated NSAIDs, including TIVORBEX, may delay or prevent rupture of ovarian follicles, which has been associated with reversible infertility in some women. Published animal studies have shown that administration of prostaglandin synthesis inhibitors has the potential to disrupt prostaglandin-mediated follicular rupture required for ovulation. Small studies in women treated with NSAIDs have also shown a reversible delay in ovulation. Consider withdrawal of NSAIDs, including TIVORBEX, in women who have difficulties conceiving or who are undergoing investigation of infertility.

8.4 Pediatric Use

The safety and effectiveness of TIVORBEX in pediatric patients 17 years of age and younger has not been established.

8.5 Geriatric Use

Elderly patients, compared to younger patients, are at greater risk for NSAID-associated serious cardiovascular, gastrointestinal, and/or renal adverse reactions. If the anticipated benefit for the elderly patient outweighs these potential risks, start dosing at the low end of the dosing range, and monitor patients for adverse effects [see Warnings and Precautions (5.1, 5.2, 5.3, 5.6, 5.13)].

Indomethacin may cause confusion or rarely, psychosis [see Adverse Reactions (6.1)]; physicians should remain alert to the possibility of such adverse effects in the elderly.

Indomethacin and its metabolites are known to be substantially excreted by the kidneys, and the risk of adverse reactions to this drug may be greater in patients with impaired renal function. Because elderly patients are more likely to have decreased renal function, use caution in this patient population, and it may be useful to monitor renal function [see Clinical Pharmacology (12.3)].

10 OVERDOSAGE

Symptoms following acute NSAID overdosages have been typically limited to lethargy, drowsiness, nausea, vomiting, and epigastric pain, which have been generally reversible with supportive care. Gastrointestinal bleeding has occurred. Hypertension, acute renal failure, respiratory depression, and coma have occurred, but were rare [see Warnings and Precautions (5.1, 5.2, 5.4,5.6)].

Manage patients with symptomatic and supportive care following an NSAID overdosage. There are no specific antidotes. Consider emesis and/or activated charcoal (60 to 100 grams in adults, 1 to 2 grams per kg of body weight in pediatric patients) and/or osmotic cathartic in symptomatic patients seen within four hours of ingestion or in patients with a large overdosage (5 to 10 times the recommended dosage). Forced diuresis, alkalinization of urine, hemodialysis, or hemoperfusion may not be useful due to high protein binding.

For additional information about overdosage treatment contact a poison control center (1-800-222-1222).

11 DESCRIPTION

TIVORBEX (indomethacin) capsule is a nonsteroidal anti-inflammatory drug, available as hard gelatin capsules of 20 mg and 40 mg for oral administration. The chemical name is 1-(4-chlorobenzoyl)-5-methoxy-2-methyl-1H-indole-3-acetic acid. The molecular weight is 357.8. Its molecular formula is C19H16ClNO4, and it has the following chemical structure.

Indomethacin is a white to yellow crystalline powder. It is practically insoluble in water and sparingly soluble in alcohol. Indomethacin has a pKa of 4.5 and is stable in neutral or slightly acidic media and decomposes in strong alkali.

The inactive ingredients in TIVORBEX include: lactose monohydrate, sodium lauryl sulfate, microcrystalline cellulose, croscarmellose sodium and sodium stearyl fumarate. The capsule shells contain gelatin, titanium dioxide, and dyes FD&C blue #1, FD&C blue #2 and FD&C red #40. The imprinting on the gelatin capsules is white edible ink. The 20 mg capsules have a dark blue body imprinted with IP-201 and light blue cap imprinted with 20 mg in white ink. The 40 mg capsules have a dark blue body imprinted with IP-202 and blue cap imprinted with 40 mg in white ink.

12 CLINICAL PHARMACOLOGY

12.1 Mechanism of Action

Indomethacin has analgesic, anti-inflammatory, and antipyretic properties.

The mechanism of action of TIVORBEX, like that of other NSAIDs, is not completely understood but involves inhibition of cyclooxygenase (COX-1 and COX-2).

Indomethacin is a potent inhibitor of prostaglandin synthesis in vitro. Indomethacin concentrations reached during therapy have produced in vivo effects. Prostaglandins sensitize afferent nerves and potentiate the action of bradykinin in inducing pain in animal models. Prostaglandins are mediators of inflammation. Because indomethacin is an inhibitor of prostaglandin synthesis, its mode of action may be due to a decrease of prostaglandins in peripheral tissues.

12.3 Pharmacokinetics

The relative bioavailability of TIVORBEX 40 mg capsules was compared to indomethacin immediate-release (IR) capsules 50 mg in 38 healthy subjects under fasted conditions in a single-dose crossover study.

TIVORBEX (indomethacin) 40 mg capsules do not result in an equivalent systemic exposure to 50 mg indomethacin IR capsules.

When taken under fasted conditions, a 20% lower dose of indomethacin in TIVORBEX 40 mg capsules resulted in a 21% lower mean systemic exposure (AUCinf) and an equivalent mean peak concentration (Cmax) compared to 50 mg indomethacin IR capsules. The median time to reach peak concentrations (Tmax) was 1.67 hours and 2.02 hours for TIVORBEX capsules and Indomethacin IR capsules, respectively.

Absorption

Similar to indomethacin IR capsules, following single oral doses of TIVORBEX capsules 20 mg or 40 mg, indomethacin is readily absorbed. TIVORBEX Capsules attained peak plasma concentrations of approximately 1.2 and 2.4 mcg/mL, respectively, at 1.67 hours. Indomethacin is virtually 100% bioavailable, with 90% of the dose absorbed within 4 hours following dosing.

Administration of TIVORBEX Capsules 20 mg and 40 mg was associated with dose proportional pharmacokinetics.

Taking TIVORBEX with food causes a significant decrease in the rate but not the overall extent of systemic absorption of indomethacin compared to taking TIVORBEX on an empty stomach. TIVORBEX capsules results in 46% lower Cmax, 9% lower AUCinf, and 1.33 hours delayed Tmax (1.67 hours during fasted versus 3.00 hours during fed) under the fed condition compared to the fasted condition. Based on the food effect evaluation on the indomethacin IR capsules, the effect of food on indomethacin pharmacokinetics is comparable between TIVORBEX capsules and indomethacin IR capsules.

Distribution

Indomethacin is highly bound to protein in plasma (about 99%) over the expected range of therapeutic plasma concentrations. Indomethacin crosses the blood-brain barrier and the placenta, and appears in breast milk.

Elimination

Metabolism

Indomethacin exists in the plasma as the parent drug and its desmethyl, desbenzoyl, and desmethyldesbenzoyl metabolites, all in the unconjugated form. Appreciable formation of glucuronide conjugates of each metabolite and of indomethacin are formed.

Excretion

Indomethacin is eliminated via metabolism and subsequent renal and biliary excretion. Indomethacin undergoes appreciable enterohepatic circulation. About 60% of an oral dose is recovered in urine as drug and metabolites (26% as indomethacin and its glucuronide), and 33% is recovered in feces (1.5% as indomethacin). The mean half-life of indomethacin from TIVORBEX capsules 40 mg is 7.6 hours and is comparable to indomethacin IR capsules 50 mg (7.2 hours).

Specific Populations

Pediatric: The pharmacokinetics of TIVORBEX has not been investigated in pediatric patients.

Race: Pharmacokinetic differences due to race have not been identified.

Hepatic Impairment: The pharmacokinetics of TIVORBEX has not been investigated in patients with hepatic impairment.

Renal Impairment: The pharmacokinetics of TIVORBEX has not been investigated in patients with renal impairment [see Warnings and Precautions (5.6)].

Drug Interaction Studies

Aspirin:

In a study in normal volunteers, it was found that chronic concurrent administration of 3.6 g of aspirin per day decreases indomethacin blood levels approximately 20% [see Drug Interactions (7)].

When NSAIDs were administered with aspirin, the protein binding of NSAIDs were reduced, although the clearance of free NSAID was not altered. The clinical significance of this interaction is not known. See Table 2 for clinically significant drug interactions of NSAIDs with aspirin [see Drug Interactions (7)].

Diflunisal:

In normal volunteers receiving indomethacin, the administration of diflunisal decreased the renal clearance and significantly increased the plasma levels of indomethacin [see Drug Interactions (7)].

13 NONCLINICAL TOXICOLOGY

13.1 Carcinogenesis, Mutagenesis, Impairment of Fertility

Carcinogenesis

In an 81-week chronic oral toxicity study in the rat at doses up to 1 mg/kg/day (0.08 times the MRHD on a mg/m^2 basis), indomethacin had no tumorigenic effect. Indomethacin produced no neoplastic or hyperplastic changes related to treatment in carcinogenic studies in the rat (dosing period 73 to 110 weeks) and the mouse (dosing period 62 to 88 weeks) at doses up to 1.5 mg/kg/day (0.06 times [mice] and 0.12 times [rats] the MRHD on a mg/m^2 basis, respectively).

Mutagenesis

Indomethacin did not have any mutagenic effect in in vitro bacterial tests and a series of in vivo tests including the host-mediated assay, sex-linked recessive lethals in Drosophila, and the micronucleus test in mice.

Impairment of Fertility

Indomethacin at dosage levels up to 0.5 mg/kg/day had no effect on fertility in mice in a two generation reproduction study (0.02 times the MRHD on a mg/m^2 basis) or a two litter reproduction study in rats (0.04 times the MRHD on a mg/m^2 basis).

14 CLINICAL STUDIES

The efficacy of TIVORBEX for the treatment of acute pain was demonstrated in two multicenter, randomized, double-blind, placebo-controlled, parallel arm studies comparing TIVORBEX 20 mg three times daily, 40 mg twice daily, 40 mg three times daily, and placebo in patients with pain following bunionectomy (Study 1 and Study 2). The two studies enrolled a total of 835 patients with a mean age of 40 years (range 18 to 68 years) a minimal pain intensity rating of at least 40 mm on a 100-mm visual analog scale (VAS) during the 9-hour period after discontinuation of the anesthetic block following bunionectomy surgery. Patients were randomized equally across the treatment groups.

The mean pain intensity measured by VAS at baseline for all treatment groups in both studies ranged from 71 to 74 mm. One tablet of hydrocodone/acetaminophen 10 mg/325 mg was permitted every 4 to 6 hours as rescue medication. There was a greater use of concomitant opioid rescue medication in placebo-treated patients than in TIVORBEX-treated patients. In Study 1, 89% of patients in the TIVORBEX 20 mg three times daily group, 90% of the patients in the TIVORBEX 40 mg twice daily group, 82% in the TIVORBEX 40 mg three times daily group, and 97% of patients in the placebo group took rescue medication for pain management during the study. In Study 2, 87% of patients in the TIVORBEX 20 mg three times daily group, 76% of the patients in the TIVORBEX 40 mg twice daily group, 80% in the TIVORBEX 40 mg three times daily group, and 89% of patients in the placebo group took rescue medication for pain management during the study.

The average pain intensities over time are depicted for the treatment groups in Figure 1 for Study 1 and Figure 2 for Study 2. In both studies, TIVORBEX Capsules 20 mg three times daily, 40 mg twice daily and 40 mg three times daily, demonstrated efficacy in pain intensity reduction compared with placebo, as measured by the sum of pain intensity difference over 0 to 48 hours after the first dose.

Figure 1 Average Pain Intensity Over 48 Hours for TIVORBEX and Placebo Groups – Study 1
Figure 2 Average Pain Intensity Over 48 Hours for TIVORBEX and Placebo Groups – Study 2

16 HOW SUPPLIED/STORAGE AND HANDLING

TIVORBEX (indomethacin) are supplied as:

- 20 mg, dark blue body and light blue cap (imprinted IP-201 on the body and 20 mg on the cap in white ink)
  • NDC 42211-201-23, Bottles of 30 capsules
  • NDC 42211-201-29, Bottles of 90 capsules
- 40 mg, dark blue body and blue cap (imprinted IP-202 on the body and 40 mg on the cap in white ink)
  • NDC 42211-202-23, Bottles of 30 capsules
  • NDC 42211-202-29, Bottles of 90 capsules

Storage

Store at room temperature 20°C to 25°C (68°F to 77°F); excursions permitted between 15°C to 30°C (59°F to 86°F) [see USP Controlled Room Temperature].

Store in the original container and keep the bottle tightly closed to protect from moisture and light. Dispense in a tight container if package is subdivided.

17 PATIENT COUNSELING INFORMATION

Advise the patient to read the FDA-approved patient labeling (Medication Guide) that accompanies each prescription dispensed. Inform patients, families, or their caregivers of the following information before initiating therapy with TIVORBEX and periodically during the course of ongoing therapy.

Cardiovascular Thrombotic Events

Advise patients to be alert for the symptoms of cardiovascular thrombotic events, including chest pain, shortness of breath, weakness, or slurring of speech, and to report any of these symptoms to their health care provider immediately [see Warnings and Precautions (5.1)].

Gastrointestinal Bleeding, Ulceration, and Perforation

Advise patients to report symptoms of ulcerations and bleeding, including epigastric pain, dyspepsia, melena, and hematemesis to their health care provider. In the setting of concomitant use of low-dose aspirin for cardiac prophylaxis, inform patients of the increased risk for and the signs and symptoms of GI bleeding [see Warnings and Precautions (5.2)].

Hepatotoxicity

Inform patients of the warning signs and symptoms of hepatotoxicity (e.g., nausea, fatigue, lethargy, pruritus, diarrhea, jaundice, right upper quadrant tenderness, and “flu-like” symptoms). If these occur, instruct patients to stop TIVORBEX and seek immediate medical therapy [see Warnings and Precautions (5.3)].

Heart Failure and Edema

Advise patients to be alert for the symptoms of congestive heart failure including shortness of breath, unexplained weight gain, or edema and to contact their healthcare provider if such symptoms occur [see Warnings and Precautions (5.5)].

Anaphylactic Reactions

Inform patients of the signs of an anaphylactic reaction (e.g., difficulty breathing, swelling of the face or throat). Instruct patients to seek immediate emergency help if these occur [see Contraindications (4) and Warnings and Precautions (5.7)].

Serious Skin Reactions

Advise patients to stop TIVORBEX immediately if they develop any type of rash and to contact their healthcare provider as soon as possible [see Warnings and Precautions (5.9)].

Female Fertility

Advise females of reproductive potential who desire pregnancy that NSAIDs, including TIVORBEX, may be associated with a reversible delay in ovulation [see Use in Specific Populations (8.3)].

Fetal Toxicity

Inform pregnant women to avoid use of TIVORBEX and other NSAIDs starting at 30 weeks gestation because of the risk of the premature closing of the fetal ductus arteriosus [see Warnings and Precautions (5.10) and Use in Specific Populations (8.1)].

Avoid Concomitant Use of NSAIDs

Inform patients that the concomitant use of TIVORBEX with other NSAIDs or salicylates (e.g., diflunisal, salsalate) is not recommended due to the increased risk of gastrointestinal toxicity, and little or no increase in efficacy [see Warnings and Precautions (5.2) and Drug Interactions (7)]. Alert patients that NSAIDs may be present in “over the counter” medications for treatment of colds, fever, or insomnia.

Use of NSAIDs and Low-Dose Aspirin

Inform patients not to use low-dose aspirin concomitantly with TIVORBEX until they talk to their healthcare provider [see Drug Interactions (7)].

Manufactured (under license from iCeutica Pty Ltd.) for and Distributed by:

Iroko Pharmaceuticals, LLC

Philadelphia, PA 19112

Issued: January 2018

Medication Guide for Nonsteroidal Anti-inflammatory Drugs (NSAIDs)

What is the most important information I should know about medicines called Nonsteroidal Anti-inflammatory Drugs (NSAIDs)?
NSAIDs can cause serious side effects, including:

- Increased risk of a heart attack or stroke that can lead to death. This risk may happen early in treatment and may increase:
  ○ with increasing doses of NSAIDs
  ○ with longer use of NSAIDs

Do not take NSAIDs right before or after a heart surgery called a “coronary artery bypass graft (CABG)."
Avoid taking NSAIDs after a recent heart attack, unless your healthcare provider tells you to. You may have an increased risk of another heart attack if you take NSAIDs after a recent heart attack.

- Increased risk of bleeding, ulcers, and tears (perforation) of the esophagus (tube leading from the mouth to the stomach), stomach and intestines:
  ○ anytime during use
  ○ without warning symptoms
  ○ that may cause death

The risk of getting an ulcer or bleeding increases with:

○ past history of stomach ulcers, or stomach or intestinal bleeding with use of NSAIDs

○ taking medicines called “corticosteroids”, “anticoagulants”, “SSRIs”, or “SNRIs”

○ increasing doses of NSAIDs

○ older age

○ longer use of NSAIDs

○ poor health

○ smoking

○ advanced liver disease

○ drinking alcohol

○ bleeding problems

NSAIDs should only be used:
○ exactly as prescribed
○ at the lowest dose possible for your treatment
○ for the shortest time needed

What are NSAIDs?
NSAIDs are used to treat pain and redness, swelling, and heat (inflammation) from medical conditions such as different types of arthritis, menstrual cramps, and other types of short-term pain.

Who should not take NSAIDs?
Do not take NSAIDs:

- if you have had an asthma attack, hives, or other allergic reaction with aspirin or any other NSAIDs.
- right before or after heart bypass surgery.

Before taking NSAIDs, tell your healthcare provider about all of your medical conditions, including if you:

- have liver or kidney problems
- have high blood pressure
- have asthma
- are pregnant or plan to become pregnant. Talk to your healthcare provider if you are considering taking NSAIDs during pregnancy. You should not take NSAIDs after 29 weeks of pregnancy.
- are breastfeeding or plan to breast feed.

Tell your healthcare provider about all of the medicines you take, including prescription or over-the-counter medicines, vitamins or herbal supplements. NSAIDs and some other medicines can interact with each other and cause serious side effects. Do not start taking any new medicine without talking to your healthcare provider first.

What are the possible side effects of NSAIDs?
NSAIDs can cause serious side effects, including:
See “What is the most important information I should know about medicines called Nonsteroidal Anti-inflammatory Drugs (NSAIDs)?”

- new or worse high blood pressure
- heart failure
- liver problems including liver failure
- kidney problems including kidney failure
- low red blood cells (anemia)
- life-threatening skin reactions
- life-threatening allergic reactions
- Other side effects of NSAIDs include: stomach pain, constipation, diarrhea, gas, heartburn, nausea, vomiting, and dizziness.

Get emergency help right away if you get any of the following symptoms:

• shortness of breath or trouble breathing

• slurred speech

• chest pain

• swelling of the face or throat

• weakness in one part or side of your body

Stop taking your NSAID and call your healthcare provider right away if you get any of the following symptoms:

• nausea

• vomit blood

• more tired or weaker than usual

• there is blood in your bowel movement or it is black and sticky like tar

• diarrhea

• unusual weight gain

• itching

• skin rash or blisters with fever

• your skin or eyes look yellow

• swelling of the arms, legs, hands and feet

• indigestion or stomach pain

• indigestion or stomach pain
• flu-like symptoms

If you take too much of your NSAID, call your healthcare provider or get medical help right away.
These are not all the possible side effects of NSAIDs. For more information, ask your healthcare provider or pharmacist about NSAIDs.
Call your doctor for medical advice about side effects. You may report side effects to FDA at 1-800-FDA-1088.

Other information about NSAIDs

- Aspirin is an NSAID but it does not increase the chance of a heart attack. Aspirin can cause bleeding in the brain, stomach, and intestines. Aspirin can also cause ulcers in the stomach and intestines.
- Some NSAIDs are sold in lower doses without a prescription (over-the-counter). Talk to your healthcare provider before using over-the-counter NSAIDs for more than 10 days.

General information about the safe and effective use of NSAIDs
Medicines are sometimes prescribed for purposes other than those listed in a Medication Guide. Do not use NSAIDs for a condition for which it was not prescribed. Do not give NSAIDs to other people, even if they have the same symptoms that you have. It may harm them.
If you would like more information about NSAIDs, talk with your healthcare provider. You can ask your pharmacist or healthcare provider for information about NSAIDs that is written for health professionals.

Manufactured (under license from iCeutica Pty Ltd) for and Distributed by:
Iroko Pharmaceuticals, LLC
One Kew Place
150 Rouse Boulevard
Philadelphia, PA 19112
For more information, go to www.iroko.com or call 1-877-757-0676.

This Medication Guide has been approved by the U.S. Food and Drug Administration. Issued or Revised: May 2016

PACKAGE LABEL

PRINCIPAL DISPLAY PANEL

NDC 42211-201-29
Tivorbex
(indomethacin) capsules
20 mg
per capsule
90 Capsules
Rx Only

PACKAGE LABEL

PRINCIPAL DISPLAY PANEL

NDC 42211-202-29
Tivorbex
(indomethacin) capsules
40 mg
per capsule
90 Capsules
Rx Only